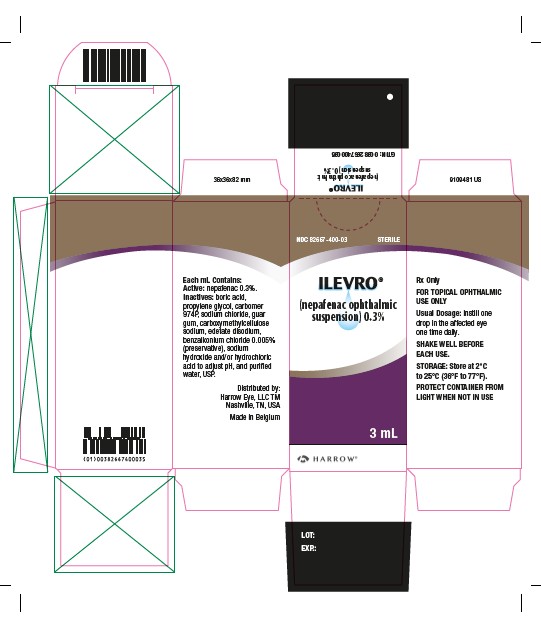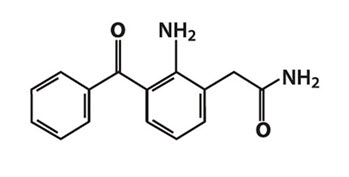 DRUG LABEL: ILEVRO
NDC: 82667-400 | Form: SUSPENSION/ DROPS
Manufacturer: Harrow Eye, LLC
Category: prescription | Type: HUMAN PRESCRIPTION DRUG LABEL
Date: 20260206

ACTIVE INGREDIENTS: NEPAFENAC 3 mg/1 mL
INACTIVE INGREDIENTS: BORIC ACID; PROPYLENE GLYCOL; CARBOMER HOMOPOLYMER TYPE B (ALLYL PENTAERYTHRITOL CROSSLINKED); SODIUM CHLORIDE; GUAR GUM; CARBOXYMETHYLCELLULOSE SODIUM; EDETATE DISODIUM; BENZALKONIUM CHLORIDE; SODIUM HYDROXIDE; HYDROCHLORIC ACID; WATER

HIGHLIGHTS OF PRESCRIBING INFORMATION

These highlights do not include all the information needed to use ILEVRO®safely and effectively. See full prescribing information for ILEVRO.
ILEVRO®(nepafenac ophthalmic suspension), topical ophthalmic
Initial U.S. Approval: 2005

1 INDICATIONS AND USAGE

ILEVRO®0.3% is a nonsteroidal, anti-inflammatory prodrug indicated for the treatment of pain and inflammation associated with cataract surgery (1).

2 DOSAGE AND ADMINISTRATION

One drop of ILEVRO®0.3% should be applied to the affected eye one-time-daily beginning 1 day prior to cataract surgery, continued on the day of surgery and through the first 2 weeks of the postoperative period. An additional drop should be administered 30 to 120 minutes prior to surgery. (2)

3 DOSAGE FORMS AND STRENGTHS

Sterile ophthalmic suspension 0.3%: 3 mL in a 4 mL bottle. (3)

4 CONTRAINDICATIONS

Hypersensitivity to any of the ingredients in the formula or to other non-steroidal anti-inflammatory drugs (NSAIDS). (4)

5 WARNINGS AND PRECAUTIONS

- Increased bleeding time due to interference with thrombocyte aggregation (5.1)
- Delayed healing (5.2)
- Corneal effects including keratitis (5.3)

6 ADVERSE REACTIONS

Most common adverse reactions (5% to 10%) are capsular opacity, decreased visual acuity, foreign body sensation, increased intraocular pressure, and sticky sensation. (6.1)

To report SUSPECTED ADVERSE REACTIONS, contact Harrow Eye, LLC at 1-833-4HARROW or FDA at 1-800-FDA-1088 or www.fda.gov/medwatch.

FULL PRESCRIBING INFORMATION

1 INDICATIONS AND USAGE

ILEVRO®0.3% is indicated for the treatment of pain and inflammation associated with cataract surgery.

2 DOSAGE AND ADMINISTRATION

2.1 Recommended Dosing

One drop of ILEVRO®0.3% should be applied to the affected eye one time daily beginning 1 day prior to cataract surgery, continued on the day of surgery and through the first 2 weeks of the postoperative period. An additional drop should be administered 30 to 120 minutes prior to surgery.

2.2 Use with Other Topical Ophthalmic Medications

ILEVRO®0.3% may be administered in conjunction with other topical ophthalmic medications such as beta-blockers, carbonic anhydrase inhibitors, alpha-agonists, cycloplegics, and mydriatics.

If more than one topical ophthalmic medication is being used, the medicines must be administered at least 5 minutes apart.

3 DOSAGE FORMS AND STRENGTHS

Sterile ophthalmic suspension 0.3%: 1.7 mL in a 4 mL bottle and 3 mL in a 4 mL bottle.

4 CONTRAINDICATIONS

ILEVRO®0.3% is contraindicated in patients with previously demonstrated hypersensitivity to any of the ingredients in the formula or to other nonsteroidal anti-inflammatory drugs (NSAIDs).

5 WARNINGS AND PRECAUTIONS

5.1 Increased Bleeding Time

With some NSAIDs including ILEVRO®0.3%, there exists the potential for increased bleeding time due to interference with thrombocyte aggregation. There have been reports that ocularly applied nonsteroidal anti-inflammatory drugs may cause increased bleeding of ocular tissues (including hyphema) in conjunction with ocular surgery.

It is recommended that ILEVRO®0.3% be used with caution in patients with known bleeding tendencies or who are receiving other medications which may prolong bleeding time.

5.2 Delayed Healing

Topical NSAIDs including ILEVRO®0.3%, may slow or delay healing. Topical corticosteroids are also known to slow or delay healing. Concomitant use of topical NSAIDs and topical steroids may increase the potential for healing problems.

5.3 Corneal Effects

Use of topical NSAIDs may result in keratitis. In some susceptible patients, continued use of topical NSAIDs may result in epithelial breakdown, corneal thinning, corneal erosion, corneal ulceration, or corneal perforation. These events may be sight threatening. Patients with evidence of corneal epithelial breakdown should immediately discontinue use of topical NSAIDs including ILEVRO®0.3% and should be closely monitored for corneal health.

Postmarketing experience with topical NSAIDs suggests that patients with complicated ocular surgeries, corneal denervation, corneal epithelial defects, diabetes mellitus, ocular surface diseases (e.g., dry eye syndrome), rheumatoid arthritis, or repeat ocular surgeries within a short period of time may be at increased risk for corneal adverse events, which may become sight threatening. Topical NSAIDs should be used with caution in these patients.

Postmarketing experience with topical NSAIDs also suggests that use more than 1 day prior to surgery or use beyond 14 days post-surgery may increase patient risk and severity of corneal adverse events.

5.4 Contact Lens Wear

ILEVRO®0.3% should not be administered while using contact lenses.

6 ADVERSE REACTIONS

Because clinical studies are conducted under widely varying conditions, adverse reaction rates observed in the clinical studies of a drug cannot be directly compared to the rates in the clinical studies of another drug and may not reflect the rates observed in practice.

6.1 Serious and Otherwise Important Adverse Reactions

The following adverse reactions are discussed in greater detail in other sections of labeling.

- Increased Bleeding Time [see Warnings and Precautions (5.1)]
- Delayed Healing [see Warnings and Precautions (5.2)]
- Corneal Effects [see Warnings and Precautions (5.3)]

6.2 Ocular Adverse Reactions

The most frequently reported ocular adverse reactions following cataract surgery were capsular opacity, decreased visual acuity, foreign body sensation, increased intraocular pressure (IOP), and sticky sensation. These reactions occurred in approximately 5% to 10% of patients.

Other ocular adverse reactions occurring at an incidence of approximately 1% to 5% included conjunctival edema, corneal edema, dry eye, lid margin crusting, ocular discomfort, ocular hyperemia, ocular pain, ocular pruritus, photophobia, tearing, and vitreous detachment.

Some of these reactions may be the consequence of the cataract surgical procedure.

6.3 Non-Ocular Adverse Reactions

Non-ocular adverse reactions reported at an incidence of 1% to 4% included headache, hypertension, nausea/vomiting, and sinusitis.

8 USE IN SPECIFIC POPULATIONS

8.1 Pregnancy

Teratogenic Effects.

Pregnancy Category C:Reproduction studies performed with nepafenac in rabbits and rats at oral doses up to 10 mg/kg/day have revealed no evidence of teratogenicity due to nepafenac, despite the induction of maternal toxicity. At this dose, the animal plasma exposure to nepafenac and amfenac was approximately 70 and 630 times human plasma exposure at the recommended human topical ophthalmic dose for rats and 20 and 180 times human plasma exposure for rabbits, respectively. In rats, maternally toxic doses greater than or equal to 10 mg/kg were associated with dystocia, increased postimplantation loss, reduced fetal weights and growth, and reduced fetal survival.

Nepafenac has been shown to cross the placental barrier in rats. There are no adequate and well-controlled studies in pregnant women. Because animal reproduction studies are not always predictive of human response, ILEVRO®0.3% should be used during pregnancy only if the potential benefit justifies the potential risk to the fetus.

Non-teratogenic Effects

Because of the known effects of prostaglandin biosynthesis inhibiting drugs on the fetal cardiovascular system (closure of the ductus arteriosus), the use of ILEVRO®0.3% during late pregnancy should be avoided.

8.3 Nursing Mothers

Nepafenac is excreted in the milk of lactating rats. It is not known whether this drug is excreted in human milk. Because many drugs are excreted in human milk, caution should be exercised when ILEVRO®0.3% is administered to a nursing woman.

8.4 Pediatric Use

The safety and effectiveness of ILEVRO®0.3% in pediatric patients below the age of 10 years have not been established.

8.5 Geriatric Use

No overall differences in safety and effectiveness have been observed between elderly and younger patients.

11 DESCRIPTION

ILEVRO®0.3% is a sterile, topical, NSAID prodrug for ophthalmic use. Each mL of ILEVRO®0.3% contains 3 mg of nepafenac. Nepafenac is designated chemically as 2-amino-3-benzoylbenzeneacetamide with an empirical formula of C15H14N2O2. The structural formula of nepafenac is:

Nepafenac is a yellow crystalline powder. The molecular weight of nepafenac is 254.28 g/mol. ILEVRO®0.3% is supplied as a sterile, aqueous suspension with a pH approximately of 6.8.

The osmolality of ILEVRO®0.3% is approximately 300 mOsm/kg.

Each mL of ILEVRO®0.3% contains: Active:nepafenac 0.3%. Inactives:boric acid, propylene glycol, carbomer 974P, sodium chloride, guar gum, carboxymethylcellulose sodium, edetate disodium, benzalkonium chloride 0.005% (preservative), sodium hydroxide and/or hydrochloric acid to adjust pH and purified water, USP.

12 CLINICAL PHARMACOLOGY

12.1 Mechanism of Action

After topical ocular dosing, nepafenac penetrates the cornea and is converted by ocular tissue hydrolases to amfenac, a NSAID. Nepafenac and amfenac are thought to inhibit the action of prostaglandin H synthase (cyclooxygenase), an enzyme required for prostaglandin production.

12.3 Pharmacokinetics

Following bilateral topical ocular once-daily dosing of ILEVRO®0.3%, the concentrations of nepafenac and amfenac peaked at a median time of 0.5 hour and 0.75 hour, respectively on both Day 1 and Day 4. The mean steady-state Cmaxfor nepafenac and for amfenac were 0.847 ± 0.269 ng/mL and 1.13 ± 0.491 ng/mL, respectively.

Nepafenac at concentrations up to 3000 ng/mL and amfenac at concentrations up to 1000 ng/mL did not inhibit the in vitrometabolism of six specific marker substrates of cytochrome P450 (CYP) isozymes (CYP1A2, CYP2C9, CYP2C19, CYP2D6, CYP2E1, and CYP3A4). Therefore, drug-drug interactions involving CYP mediated metabolism of concomitantly administered drugs are unlikely.

13 NONCLINICAL TOXICOLOGY

13.1 Carcinogenesis, Mutagenesis, Impairment of Fertility

Nepafenac has not been evaluated in long-term carcinogenicity studies. Increased chromosomal aberrations were observed in Chinese hamster ovary cells exposed in vitroto nepafenac suspension. Nepafenac was not mutagenic in the Ames assay or in the mouse lymphoma forward mutation assay. Oral doses up to 5000 mg/kg did not result in an increase in the formation of micronucleated polychromatic erythrocytes in vivoin the mouse micronucleus assay in the bone marrow of mice.

Nepafenac did not impair fertility when administered orally to male and female rats at 3 mg/kg.

14 CLINICAL STUDIES

In two double masked, randomized clinical trials in which patients were dosed daily beginning one day prior to cataract surgery, continued on the day of surgery and for the first two weeks of the postoperative period, ILEVRO®0.3% demonstrated superior clinical efficacy compared to its vehicle in treating postoperative pain and inflammation.

Treatment effect over vehicle for resolution of ocular pain occurred as early as Day 1 post-surgery. Treatment effect over vehicle for resolution of inflammation was significantly better than vehicle in both studies at Day 7 and Day 14 post-surgery.

Table 1: Inflammation and Ocular Pain Resolution Results of Nepafenac Ophthalmic Suspension, 0.3% versus Vehicle at Day 14 Post-surgery (All-Randomized Population)
Study | Treatment | Inflammation Resolution at Postop Day 14 | Ocular Pain Resolution at Postop Day 14
Study 1 | Nepafenac ophthalmic suspension, 0.3% (n/N)(1) | 552/851 (65%) | 734/851 (86%)
Study 1 | NEVANAC (n/N)(1) | 568/845 (67%) | 737/845 (87%)
Study 1 | Vehicle (n/N)(1) | 67/211 (32%) | 98/211 (46%)
Study 1 | Difference (95% CI)(2) | 33% (26%, 40%) | 40% (32%, 47%)
Study 2 | Nepafenac ophthalmic suspension, 0.3% (n/N)(1) | 331/540 (61%) | 456/540 (84%)
Study 2 | Vehicle (n/N)(1) | 63/268 (24%) | 101/268 (38%)
Study 2 | Difference (95% CI)(2) | 38% (31%, 45%) | 47% (40%, 54%)
Abbreviation: CI, confidence interval.
(1)n/N is the ratio of those with complete resolution of anterior chamber cell and flare by the postoperative Day 14 visit over all randomized subjects.
(2)Difference is Nepafenac ophthalmic suspension, 0.3% (n/N) – vehicle. The 95% CI is derived using asymptotic approximation.

16 HOW SUPPLIED/STORAGE AND HANDLING

ILEVRO®0.3% is supplied in a white, oval, low density polyethylene dispenser with a natural low density polyethylene dispensing plug and gray polypropylene cap.

3 mL in 4 mL bottle NDC 82667-400-03

Storage:Store at 2°C to 25°C (36°F to 77°F).

Protect from light.

17 PATIENT COUNSELING INFORMATION

Slow or Delayed Healing

Inform the patient of the possibility that slow or delayed healing may occur while using NSAIDs [see Warnings and Precautions (5.2)] .

Avoiding Contamination of the Product

Instruct the patient to avoid allowing the tip of the dispensing container to contact the eye or surrounding structures because this could cause the tip to become contaminated by common bacteria known to cause ocular infections. Serious damage to the eye and subsequent loss of vision may result from using contaminated solutions.

Use of the same bottle for both eyes is not recommended with topical eye drops that are used in association with surgery.

Contact Lens Wear

ILEVRO®0.3% should not be administered while wearing contact lenses [see Warnings and Precautions (5.4)] .

Intercurrent Ocular Conditions

Advise the patient that if they develop an intercurrent ocular condition (e.g., trauma, or infection) or have ocular surgery, they should immediately seek their physician’s advice concerning the continued use of the multi-dose container [see Warnings and Precautions (5.1)] .

Concomitant Topical Ocular Therapy

If more than one topical ophthalmic medication is being used, the medicines must be administered at least 5 minutes apart [see Dosage and Administration (2.2)] .

Shake Well Before Use

Patients should be instructed to shake well before each use [see Dosage and Administration (2.1)] .

Distributed by
Harrow Eye, LLC™
Nashville, TN, USA

PRINCIPAL DISPLAY PANEL

NDC 82667-400-03

STERILE

ILEVRO®

(nepafenac ophthalmic suspension) 0.3%

3 mL

Harrow Eye, LLCTM

HARROW®